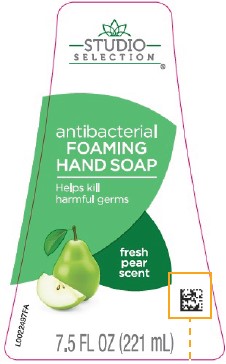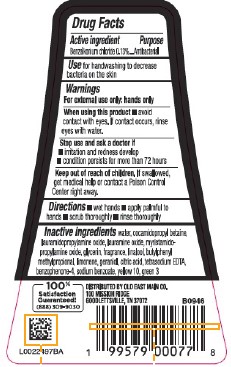 DRUG LABEL: Benzalkonium chloride
NDC: 75712-575 | Form: LIQUID
Manufacturer: Old East Main Co.
Category: otc | Type: HUMAN OTC DRUG LABEL
Date: 20260302

ACTIVE INGREDIENTS: BENZALKONIUM CHLORIDE 1.3 mg/1 mL
INACTIVE INGREDIENTS: GLYCERIN; SODIUM BENZOATE; WATER; BUTYLPHENYL METHYLPROPIONAL; LAURAMIDOPROPYLAMINE OXIDE; LIMONENE, (+)-; GERANIOL; SULISOBENZONE; MYRISTAMIDOPROPYLAMINE OXIDE; D&C YELLOW NO. 10; LAURAMINE OXIDE; EDETATE SODIUM; LINALOOL, (+)-; FD&C GREEN NO. 3; COCAMIDOPROPYL BETAINE; CITRIC ACID MONOHYDRATE

Studio Selection 575.002/575AD
Pear Foaming Antibacterial Hand Wash

Active ingredient

Benzalkonium chloride 0.13%

Purpose

Antibacterial

Use

for handwashing to decrease bacteria on the skin

Warnings

For external use only: hands only

When using this product

- avoid contact with eyes. If contact occurs, rinse eyes with water.

Stop use and ask a doctor

- irritation and redness develop
- condition persists for more than 72 hours

Keep out of reach of children.

If swallowed, get medical help or contact a Poison Control Center right away.

Directions

- wet hands
- apply palmful to hands
- scrub thoroughly
- rinse thoroughly

Inactive ingredients

water, cocamidopropyl betaine, lauramidopropylamine oxide, lauramine oxide, myristamidopropylamine oxide, glycerin, fragrance, linalool, butylphenyl methylpropional, limonene, geraniol, citric acid, tetrasodium EDTA, benzophenone-4, sodium benzoate, yellow 10, green 3

Adverse Reaction

100% Satisfaction Guaranteed!

(888) 309-9030

DISTRIBUTED BY OLD EAST MAIN CO.

100 MISSION RIDGE

GOODLETTSVILLE, TN 37072

Principal Display Panel

STUDIO SELECTION™

antibacterial

FOAMING HAND SOAP

Helps kill harmful germs

fresh pear scent

7.5 FL OZ (221 mL)